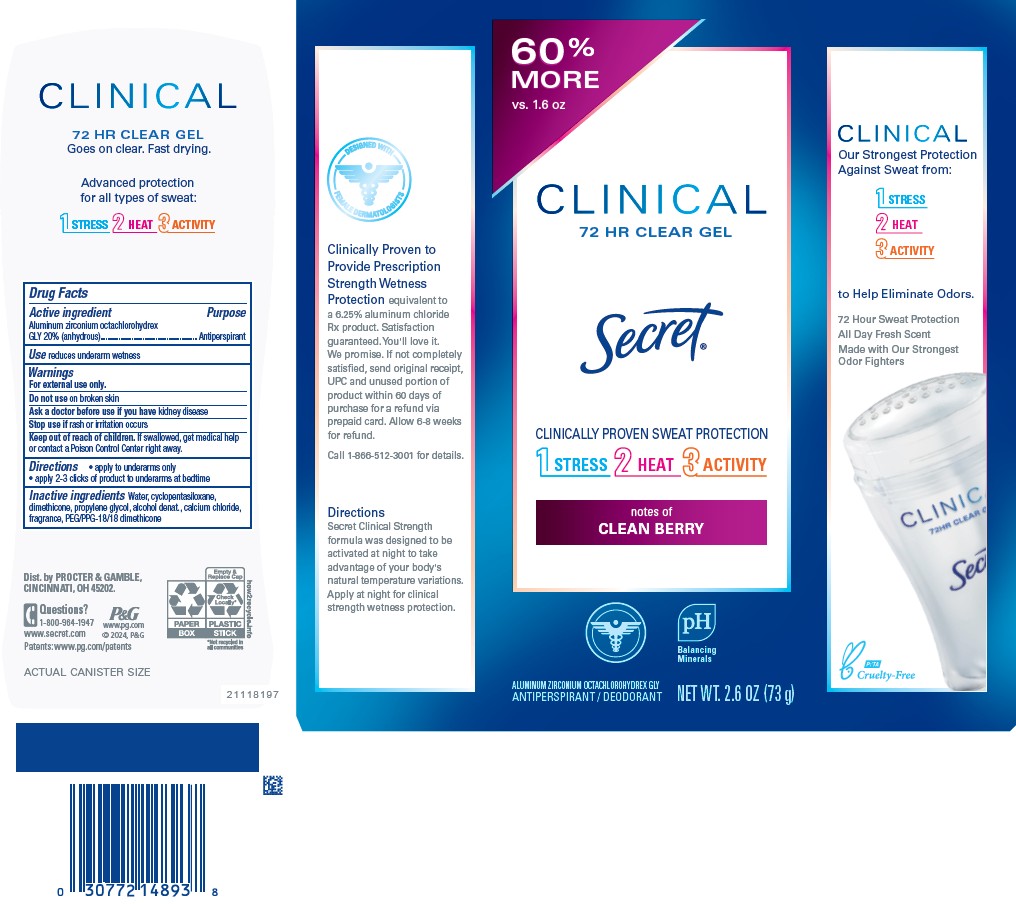 DRUG LABEL: Secret Clinical Clear Clean Berry
NDC: 84126-194 | Form: GEL
Manufacturer: The Procter & Gamble Manufacturing Company
Category: otc | Type: HUMAN OTC DRUG LABEL
Date: 20251119

ACTIVE INGREDIENTS: ALUMINUM ZIRCONIUM OCTACHLOROHYDREX GLY 20 g/100 g
INACTIVE INGREDIENTS: WATER; CYCLOPENTASILOXANE; DIMETHICONE; PROPYLENE GLYCOL; CALCIUM CHLORIDE; PEG/PPG-18/18 DIMETHICONE; ALCOHOL

Secret® Clinical Clear Gel Clean Berry

Drug Facts

Active ingredient

Aluminum zirconium octachlorohydrex Gly 20% (anhydrous)

Purpose

Antiperspirant

Use

- reduces underarm wetness

Warnings

For external use only.

Do not use on broken skin

Ask a doctor before use if you have kidney disease

Stop use if rash or irritation occurs

Keep out of reach of children. If swallowed, get medical help or contact a Poison Control Center right away.

Directions

- apply to underarms only
- apply 2-3 clicks of product to underarms at bedtime

Inactive ingredients

water, cyclopentasiloxane, dimethicone, propylene glycol, alcohol denat., calcium chloride, fragrance, PEG/PPG-18/18 dimethicone

Questions?

1-800-964-1947

Dist. by PROCTER & GAMBLE,
CINCINNATI, OH 45202.

PRINCIPAL DISPLAY PANEL - 73 g Cylinder Carton

Secret®

CLINICAL

72 HR CLEAR GEL

Clinically proven prescription sweat protection

notes of Clean Berry

aluminum zirconium octachlorohydrex GLY
antiperspirant / deodorant

NET WT. 2.6 OZ (73 g)